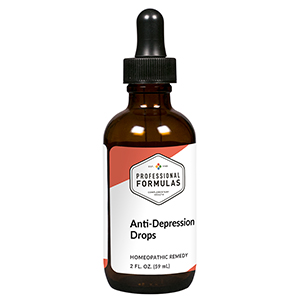 DRUG LABEL: Melancholy Drops
NDC: 63083-2002 | Form: LIQUID
Manufacturer: Professional Complementary Health Formulas
Category: homeopathic | Type: HUMAN OTC DRUG LABEL
Date: 20190815

ACTIVE INGREDIENTS: LITHIUM CARBONATE 6 [hp_X]/59 mL; BOS TAURUS BRAIN 6 [hp_X]/59 mL; SUS SCROFA PINEAL GLAND 6 [hp_X]/59 mL; GOLD 12 [hp_X]/59 mL; STRYCHNOS IGNATII SEED 12 [hp_X]/59 mL; SODIUM CHLORIDE 12 [hp_X]/59 mL; SEPIA OFFICINALIS JUICE 12 [hp_X]/59 mL; SEROTONIN 16 [hp_X]/59 mL
INACTIVE INGREDIENTS: ALCOHOL; WATER

C2

ACTIVE INGREDIENTS

Lithium carbonicum 6X
Brain 6X, 12X, 30X, 60X
Pineal 6X, 12X, 30X, 60X
Aurum metallicum 12X, 30X, 60X
Ignatia amara 12X, 30X, 60X
Natrum muriaticum 12X, 30X, 60X
Sepia 12X, 30X, 60X
Serotonin 16X

QUESTIONS

Professional Formulas

PO Box 2034 Lake Oswego, OR 97035

INDICATIONS

For the temporary relief of sadness, anxiousness, difficulty concentrating, or fatigue.*

PURPOSE

*Claims based on traditional homeopathic practice, not accepted medical evidence. Not FDA evaluated.

WARNINGS

Persistent symptoms may be a sign of a serious condition. If symptoms persist or worsen, consult a doctor. Keep out of the reach of children. In case of overdose, get medical help or contact a poison control center right away. If pregnant or breastfeeding, ask a healthcare professional before use.

Keep out of the reach of children.

PREGNANCY OR BREAST FEEDING

If pregnant or breastfeeding, ask a healthcare professional before use.

DIRECTIONS

Place drops under tongue 30 minutes before/after meals. Adults and children 12 years and over: Take 10 drops up to 3 times per day. Consult a physician for use in children under 12 years of age.

OTHER INFORMATION

Tamper resistant. If seal is broken, do not use. After opening, close container tightly and store at room temperature away from heat.

INACTIVE INGREDIENTS

20% ethanol, purified water.

LABEL

Est 1985

Professional Formulas

Complementary Health

Melancholy Drops

Homeopathic Remedy

2 FL. OZ. (59 mL)